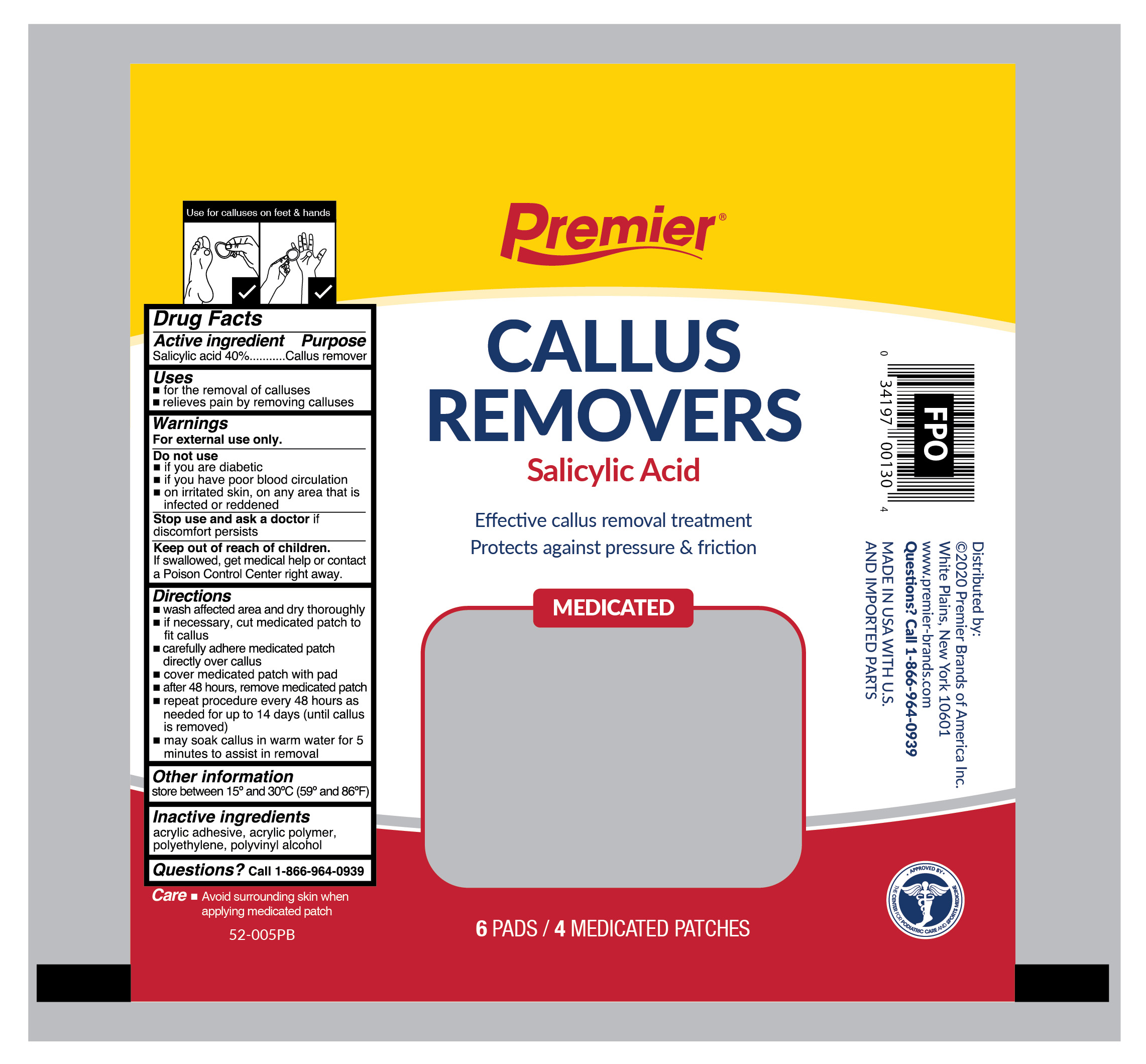 DRUG LABEL: Salicylic acid
NDC: 56104-013 | Form: PATCH
Manufacturer: Premier Brands of America Inc.
Category: otc | Type: HUMAN OTC DRUG LABEL
Date: 20251230

ACTIVE INGREDIENTS: SALICYLIC ACID 40 mg/4 1
INACTIVE INGREDIENTS: POLYVINYL ALCOHOL; HIGH DENSITY POLYETHYLENE

Premier Brands Callus Removers

Active ingredient

Salicylic acid 40%

Purpose

Callus remover

Use

- for the removal of calluses
- relieves pain by removing calluses

Warnings

For external use only.

Do not use

- if you are a diabetic
- have poor blood circulation
- on irritated skin, on any area that is infected or reddened

If discomfort persists see your doctor or podiatrist

Keep out of reach of children.

If swallowed, get medical help or contact a Poison Control Center right away.

Directions

- wash affected area and dry thoroughly
- if necessary, cut medicated patch to fit callus
- apply adhesive side down of medicated patch onto callus
- cover medicated patch with pad
- after 48 hours, remove medicated patch
- repeat procedure every 48 hours as needed for up to 14 days (until callus is removed)
- may soak callus in warm water for 5 minutes to assist in removal
- continued wearing of pad (without patch) will help prevent recurrence of calluses

Other information

store between 15°C to 30°C (59°F to 86°F)

Inactive ingredients

acrylic adhesive, acrylic polymer, polyethylene, polyvinyl alcohol

Questions?

call 1-866-964-0939

Principal Display Panel

Premier

CALLUS REMOVERS
Salicylic Acid

Effective callus removal treatment

Protects against pressure & friction

MEDICATED

6 PADS/4 MEDICATED PATCHES